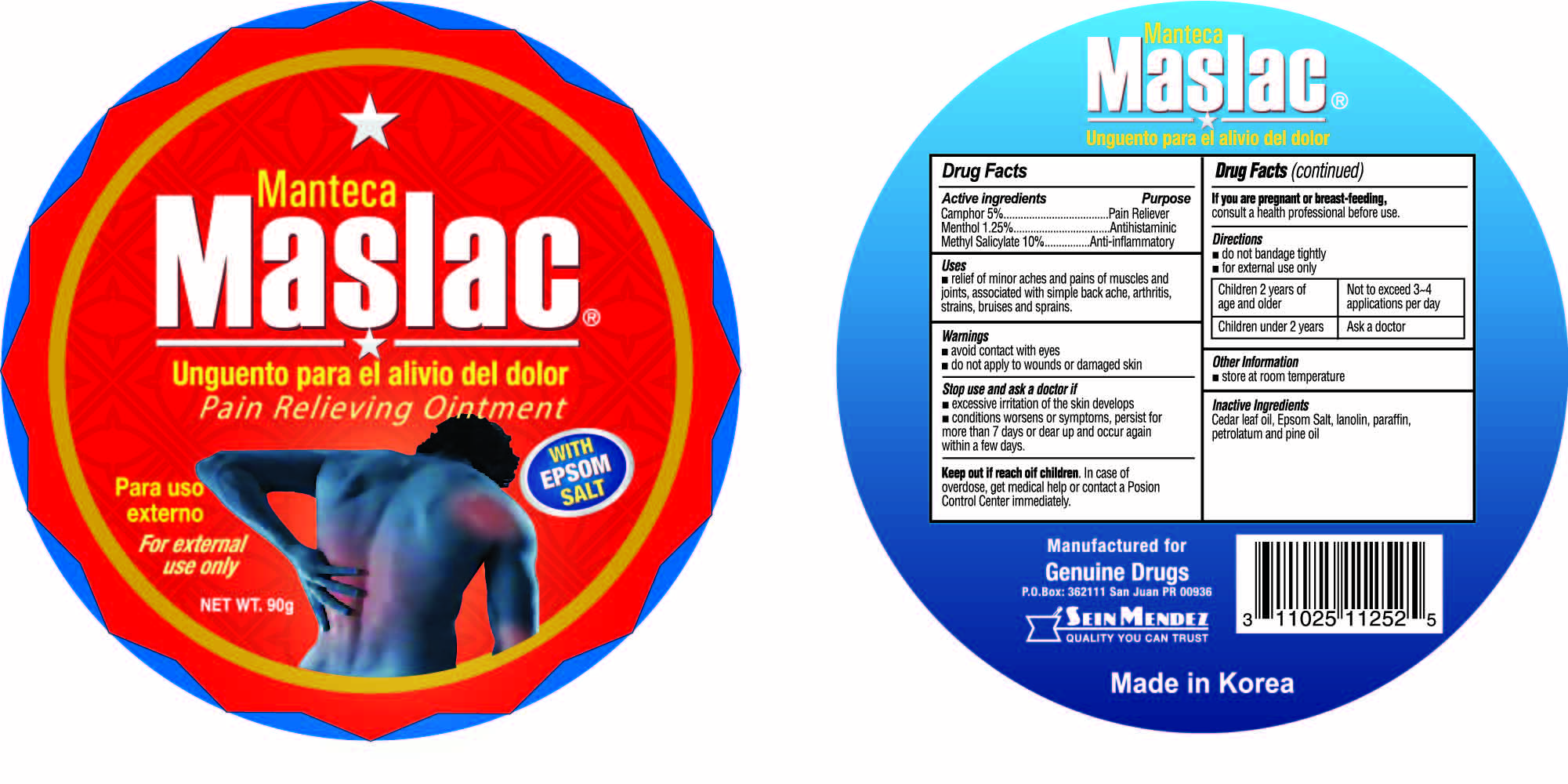 DRUG LABEL: Manteca Maslac
NDC: 69666-252 | Form: OINTMENT
Manufacturer: Genuine Drugs
Category: otc | Type: HUMAN OTC DRUG LABEL
Date: 20230217

ACTIVE INGREDIENTS: MENTHOL 1.25 g/100 g; CAMPHOR (NATURAL) 5 g/100 g; METHYL SALICYLATE 10 g/100 g
INACTIVE INGREDIENTS: PETROLATUM; cedar leaf oil; LANOLIN; WHITE PINE OIL; MAGNESIUM SULFATE, UNSPECIFIED

Manteca Maslac Pain Relieving Ointment

Warnings

- avoid contact with eyes
- do not apply to wounds or damaged skin

Keep out of reach of children

In case of overdose, get medical help or contact a Poison Control Center immediately.

Stop use and ask a doctor if

- excessive irritation of the skin develops
- conditions worsen or symptoms persist for more than 7 days or flare up and occur again within a few days

Uses

- relief of minor aches and pains of muscles and joints, associated with simple back ache, arthritis, strains, bruises and sprains.

Directions

- do not bandage tightly
- for external use only

Children 2 years of age and older | Not to exceed 3-4 application per day
Children under 2 years | Ask a doctor

Other information

- store at room temperature

Inactive Ingredients

Cedar leaf oil, Epsom Salt, lanolin, paraffin, petrolatum and pine oil

PURPOSE

Topical analgesic

Topical analgesic

Topical analgesic

Active Ingredients

Camphor 5%

Menthol 1.25%

Methyl Salicylate 10%

If you are pregnant or breast-feeding

consult a health professional before use.

package label

Maslac pain relief ointment